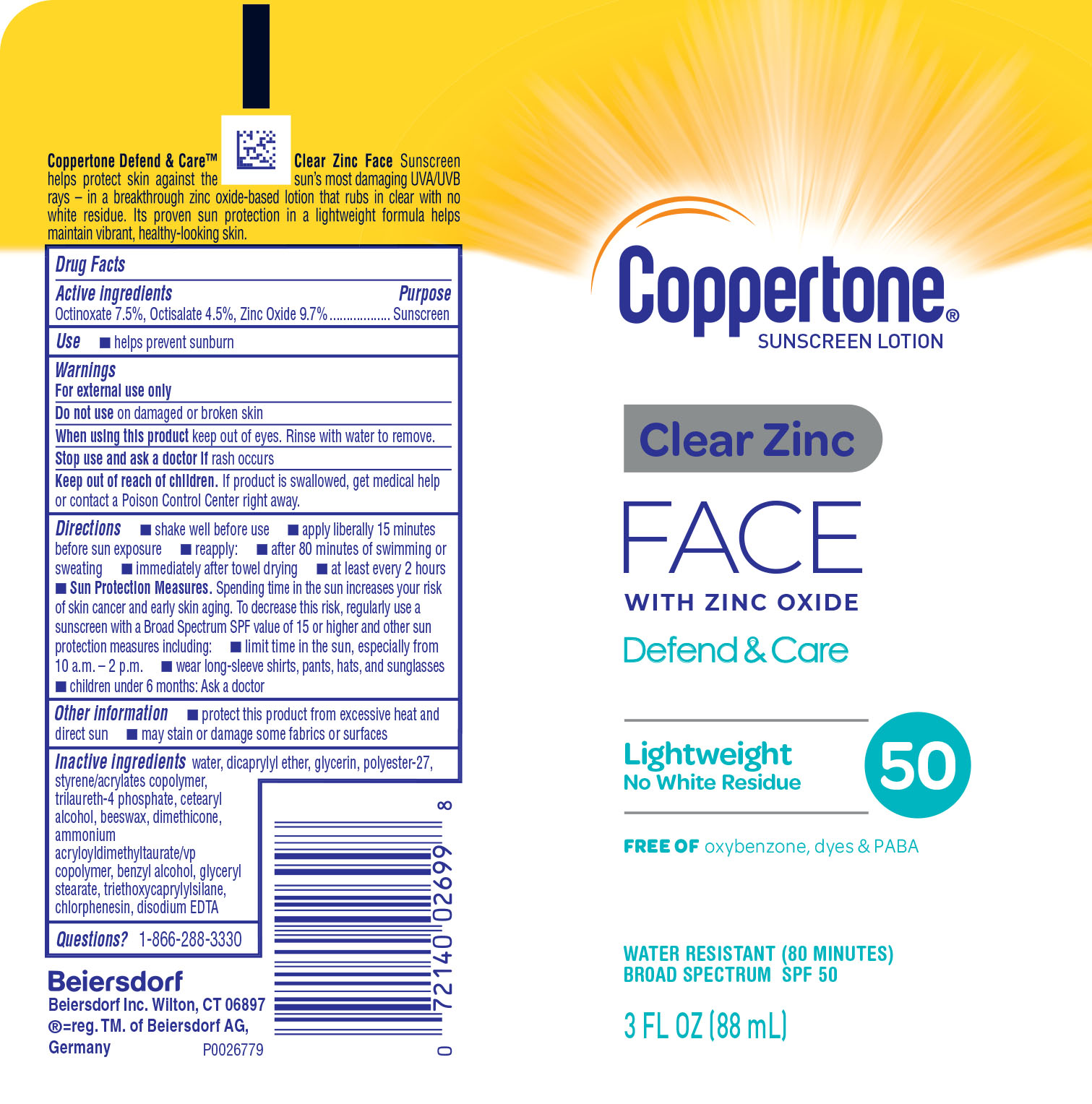 DRUG LABEL: Coppertone Defend and Clear
NDC: 66800-3641 | Form: LOTION
Manufacturer: Beiersdorf Inc
Category: otc | Type: HUMAN OTC DRUG LABEL
Date: 20251231

ACTIVE INGREDIENTS: OCTISALATE 4.5 g/100 g; ZINC OXIDE 9.7 g/100 g; OCTINOXATE 7.5 g/100 g
INACTIVE INGREDIENTS: AMMONIUM ACRYLOYLDIMETHYLTAURATE/VP COPOLYMER; BENZYL ALCOHOL; GLYCERYL STEARATE SE; TRIETHOXYCAPRYLYLSILANE; CHLORPHENESIN; CETOSTEARYL ALCOHOL; WATER; STYRENE/ACRYLAMIDE COPOLYMER (MW 500000); TRILAURETH-4 PHOSPHATE; SYNTHETIC BEESWAX; DIMETHICONE; MAGNESIUM DISODIUM EDTA; GLYCERIN; DICAPRYLYL ETHER; POLYESTER-7

D&C Clear Zinc Face SPF 50

Active ingredients

Octinoxate 7.5%, Octisalate 4.5%, Zinc Oxide 9.7%

Purpose

Sunscreen

Use

helps prevent sunburn

Warnings

For external use only

Do not useon damaged or broken skin

WHEN USING

When using this productkeep out of eyes. Rinse with water to remove.

Stop use and ask a doctor ifrash occurs

Keep out of reach of children.If product is swallowed, get medical help or contact a Poison Control Center right away.

Directions

■ shake well before use

■ apply liberally 15 minutes before sun exposure

■ reapply:

■ after 80 minutes of swimming or sweating

■ immediately after towel drying

■ at least every 2 hours

■ Sun Protection Measures.Spending time in the sun increases your risk of skin cancer and early skin aging. To decrease this risk, regularly use a sunscreen with a Broad Spectrum SPF value of 15 or higher and other sun protection measures including:

■ limit time in the sun, especially from 10 a.m. – 2 p.m.

■ wear long-sleeve shirts, pants, hats, and sunglasses

■ children under 6 months: Ask a doctor

Other information

■ protect this product from excessive heat and direct sun

■ may stain or damage some fabrics or surfaces

Inactive ingredients

water, dicaprylyl ether, glycerin, polyester-27,styrene/acrylates copolymer, trilaureth-4phosphate,cetearylalcohol,beeswax,dimethicone, ammonium acryloyldimethyltaurate/VP copolymer, benzyl alcohol,glyceryl stearate, triethoxycaprylylsilane, chlorphenesin, disodium EDTA

Questions?

1-866-288-3330

PACKAGE LABEL

CoppertoneSunscreen Lotion

Clear Zince FACE

with Zinc Oxide

Defend & Care

LightweightNo White Residue

Free ofoxybenzone, dyes & PABA

Water Resistant (80 Minutes)

Broad Specturm SPF 50

3 FL OZ (88 mL)